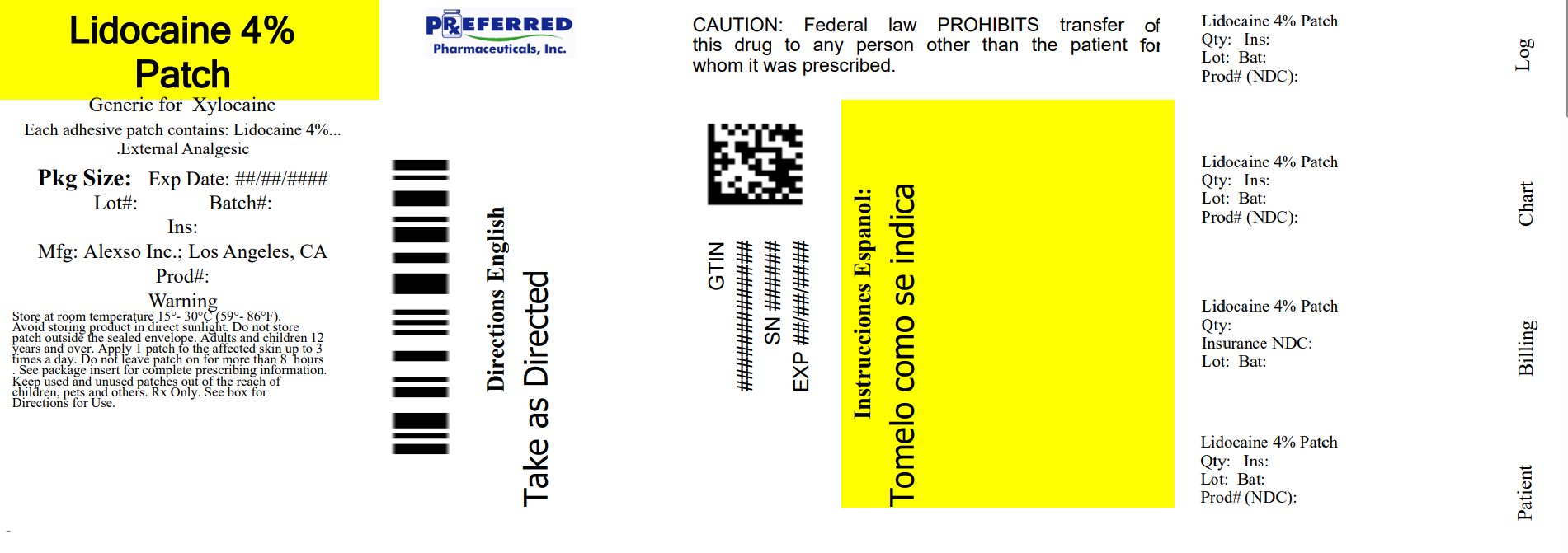 DRUG LABEL: Lidocaine
NDC: 68788-4029 | Form: PATCH
Manufacturer: Preferred Pharmaceuticals Inc.
Category: otc | Type: HUMAN OTC DRUG LABEL
Date: 20250922

ACTIVE INGREDIENTS: LIDOCAINE 4 g/1 g
INACTIVE INGREDIENTS: WATER; GLYCERIN; PROPYLENE GLYCOL; POLYSORBATE 80; TARTARIC ACID; DIHYDROXYALUMINUM AMINOACETATE; METHYLPARABEN; PEPPERMINT OIL; SODIUM POLYACRYLATE (8000 MW)

Lidocaine Patch

LIDOCAINE – Lidocaine 4% Patch

Alexso, Inc.

Disclaimer: Most OTC drugs are not reviewed and approved by FDA, however they may be marketed if they comply with applicable regulations and policies. FDA has not evaluated whether this product complies.

----------

Lidocaine 4% Patch

Drug Facts

Active ingredient

Lidocaine 4%

Purpose

External analgesic

Uses

Temporarily relieves pain and itching associated with:

• minor burns

• sunburn

• minor cuts

• scrapes

• insect bites

• minor skin irritations

Warnings

For external use only.

Read all warnings and directions before use.

Do not use

• More than one patch at a time

• On wounds or damaged skin

• With a heating pad

• If you are allergic to any ingredients of this product

Allergy Alert: if you are allergic to any inactive ingredient of this product, contact a doctor before use.

When using this product

• Use only as directed.

• Avoid contact with eyes, mucous membranes, or rashes

• Do not tightly wrap or bandage the treated area

Stop use and ask a physician:

• If pregnant or breast feeding

• If localized skin reactions occur, such as rash, itching, redness, irritation, pain, swelling, and blistering

• If condition worsens, or if symptoms persist for more than 7 days or clear up and occur again within a few days, discontinue use of this product and consult a physician.

Keep out of reach of children and pets.

If swallowed, get medical help or contact a Poison Control Center immediately.

Directions

Adults and children 12 years of age and older:

Apply 1 patch to the affected area of intact skin up to 3 times a day. Do not leave patch on for more than 8 hours at a time.

- Clean and dry the affected area.
- Open pouch and remove one patch.
- Remove any protective film and apply directly to affected area of pain. Apply immediately after removal from the protective envelope.
- Wash hands with soap and water after handling the patches.
- Reseal pouch containing unused patches after each use. Do not store patch outside the sealed envelope.
- Fold used patches so that the adhesive side sticks to itself and safely discard used patches or pieces of cut patches where children and pets cannot get to them.

Children under 12 years: Ask a physician

Other information

Store at room temperature 15°-30°C (59°-86°F)

Avoid storing product in direct sunlight and protect product from excessive moisture.

Inactive ingredients

Aqua (Deionized Water), Glycerin, Sodium Polyacrylate, Propylene Glycol, Polysorbate 80, Tartaric Acid, Dihydroxyaluminium Aminoacetate, Methylparaben, Peppermint Oil

PRINCIPAL DISPLAY PANEL

Lidocaine 4% Patch

NDC 68788-4029-1

10 Patches per Box

Alexso, Inc

Relabeled By: Preferred Pharmaceuticals Inc.